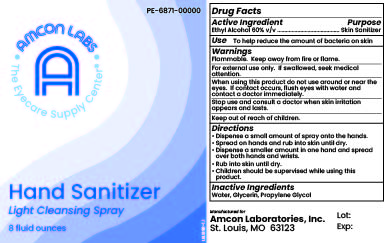 DRUG LABEL: Amcon Labs Hand Sanitizer Light Cleansing
NDC: 51801-779 | Form: SPRAY
Manufacturer: Nomax, Inc.
Category: otc | Type: HUMAN OTC DRUG LABEL
Date: 20231120

ACTIVE INGREDIENTS: ALCOHOL 600 mL/1 L
INACTIVE INGREDIENTS: GLYCERIN; PROPYLENE GLYCOL; WATER

Amcon Labs Hand Sanitizer Light Cleansing Spray

Active Ingredient

Ethyl Alcohol 60% v/v

Purpose

Skin Sanitizer

Use

To help reduce the amount of bacteria on skin

Warnings

Flammable. Keep away from fire or flame.

For external use only. If swallowed, seek medical attention.

When using this product do not use around or near the eyes. If contact occurs, flush eyes with water and contact a doctor immediately.

Stop use and consult a doctor when skin irritation appears and lasts.

Keep out of reach of children.

Directions

- Dispense a small amount of spray onto the hands.
- Spread on hands and rub into skin until dry.
- Dispense a smaller amount in one hand and spread over both hands and wrists.
- Rub into skin until dry.
- Children should be supervised while using this product.

Inactive Ingredient

Water, Glycerin, Propylene Glycol